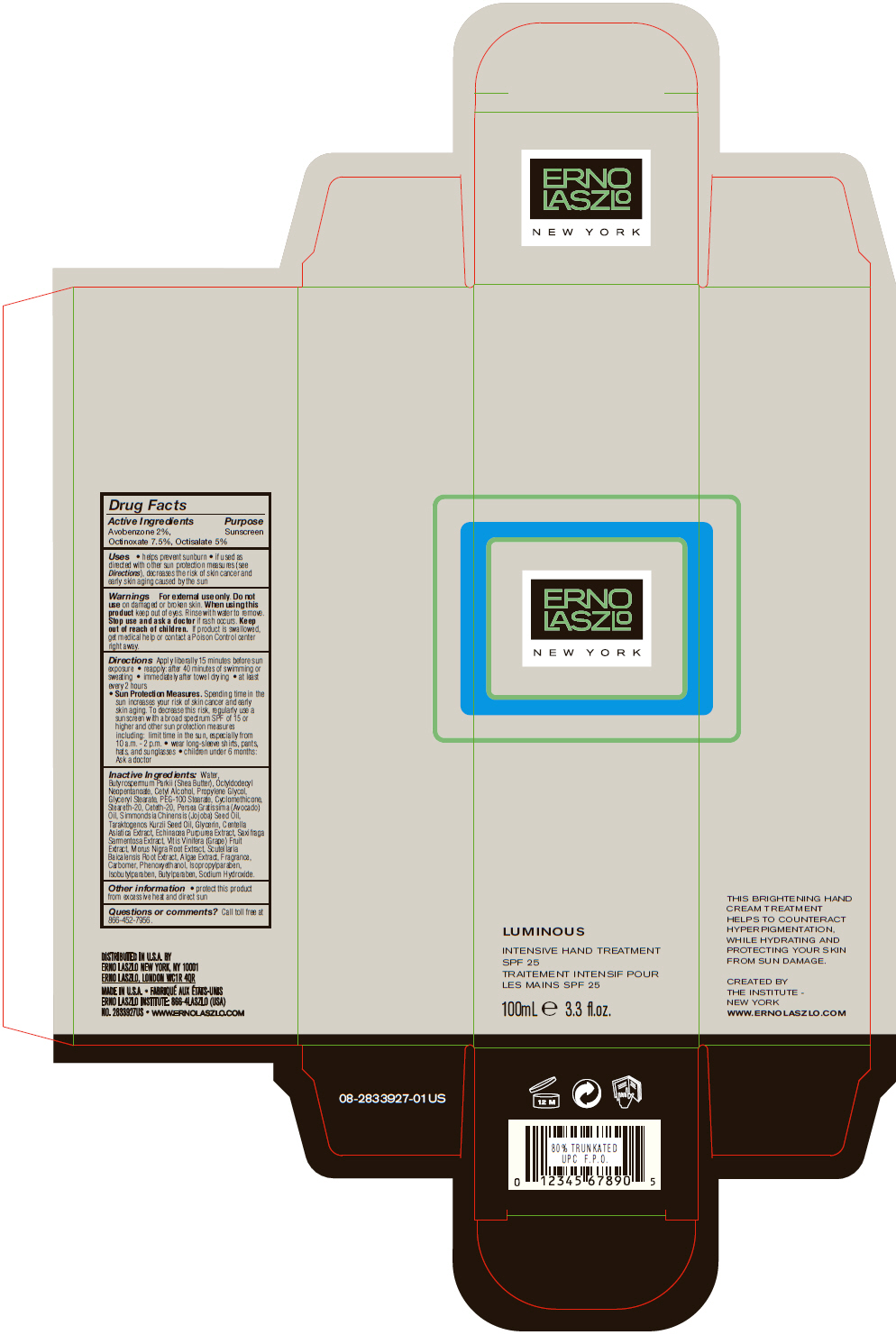 DRUG LABEL: Luminous Intensive Hand Treatment  SPF 25
NDC: 57913-2525 | Form: LOTION
Manufacturer: Erno Laszlo, Inc.
Category: otc | Type: HUMAN OTC DRUG LABEL
Date: 20130409

ACTIVE INGREDIENTS: Avobenzone 20 mg/1 mL; Octinoxate 75 mg/1 mL; Octisalate 50 mg/1 mL
INACTIVE INGREDIENTS: WATER; SHEA BUTTER; OCTYLDODECYL NEOPENTANOATE; CETYL ALCOHOL; PROPYLENE GLYCOL; GLYCERYL MONOSTEARATE; PEG-100 STEARATE; CYCLOMETHICONE; STEARETH-20; CETETH-20; AVOCADO OIL; JOJOBA OIL; HYDNOCARPUS KURZII SEED OIL; GLYCERIN; CENTELLA ASIATICA; ECHINACEA PURPUREA; SAXIFRAGA STOLONIFERA LEAF; WINE GRAPE; MORUS NIGRA ROOT; SCUTELLARIA BAICALENSIS ROOT; PHENOXYETHANOL; ISOPROPYLPARABEN; ISOBUTYLPARABEN; BUTYLPARABEN; SODIUM HYDROXIDE

Luminous Intensive Hand Treatment SPF 25

Drug Facts

Active Ingredients

Avobenzone 2%, Octinoxate 7.5%, Octisalate 5%

Purpose

Sunscreen

Uses

- helps prevent sunburn
- if used as directed with other sun protection measures (see Directions), decreases the risk of skin cancer and early skin aging caused by the sun

Warnings

For external use only.

Do not use on damaged or broken skin.

When using this product keep out of eyes. Rinse with water to remove.

Stop use and ask a doctor if rash occurs.

Keep out of reach of children. If product is swallowed, get medical help or contact a Poison Control center right away.

Directions

Apply liberally 15 minutes before sun exposure

- reapply: after 40 minutes of swimming or sweating
- immediately after towel drying
- at least every 2 hours
- Sun Protection Measures. Spending time in the sun increases your risk of skin cancer and early skin aging. To decrease this risk, regularly use a sunscreen with a broad spectrum SPF of 15 or higher and other sun protection measures including: limit time in the sun, especially from 10 a.m. - 2 p.m.
  - wear long-sleeve shirts, pants, hats, and sunglasses
  - children under 6 months: Ask a doctor

Inactive Ingredients

Water, Butyrospermum Parkii (Shea Butter), Octyldodecyl Neopentanoate, Cetyl Alcohol, Propylene Glycol, Glyceryl Stearate, PEG-100 Stearate, Cyclomethicone, Steareth-20, Ceteth-20, Persea Gratissima (Avocado) Oil, Simmondsia Chinensis (Jojoba) Seed Oil, Taraktogenos Kurzii Seed Oil, Glycerin, Centella Asiatica Extract, Echinacea Purpurea Extract, Saxifraga Sarmentosa Extract, Vitis Vinifera (Grape) Fruit Extract, Morus Nigra Root Extract, Scutellaria Baicalensis Root Extract, Algae Extract, Fragrance, Carbomer, Phenoxyethanol, Isopropylparaben, Isobutylparaben, Butylparaben, Sodium Hydroxide.

Other information

- protect this product from excessive heat and direct sun

Questions or comments?

Call toll free at 866-452-7956.

DISTRIBUTED IN U.S.A. BY ERNO LASZLO NEW YORK, NY 10001

PRINCIPAL DISPLAY PANEL - 100 mL Tube Carton

ERNO
LASZLO

NEW YORK

LUMINOUS

INTENSIVE HAND TREATMENT
SPF 25

100mL e 3.3 fl.oz.